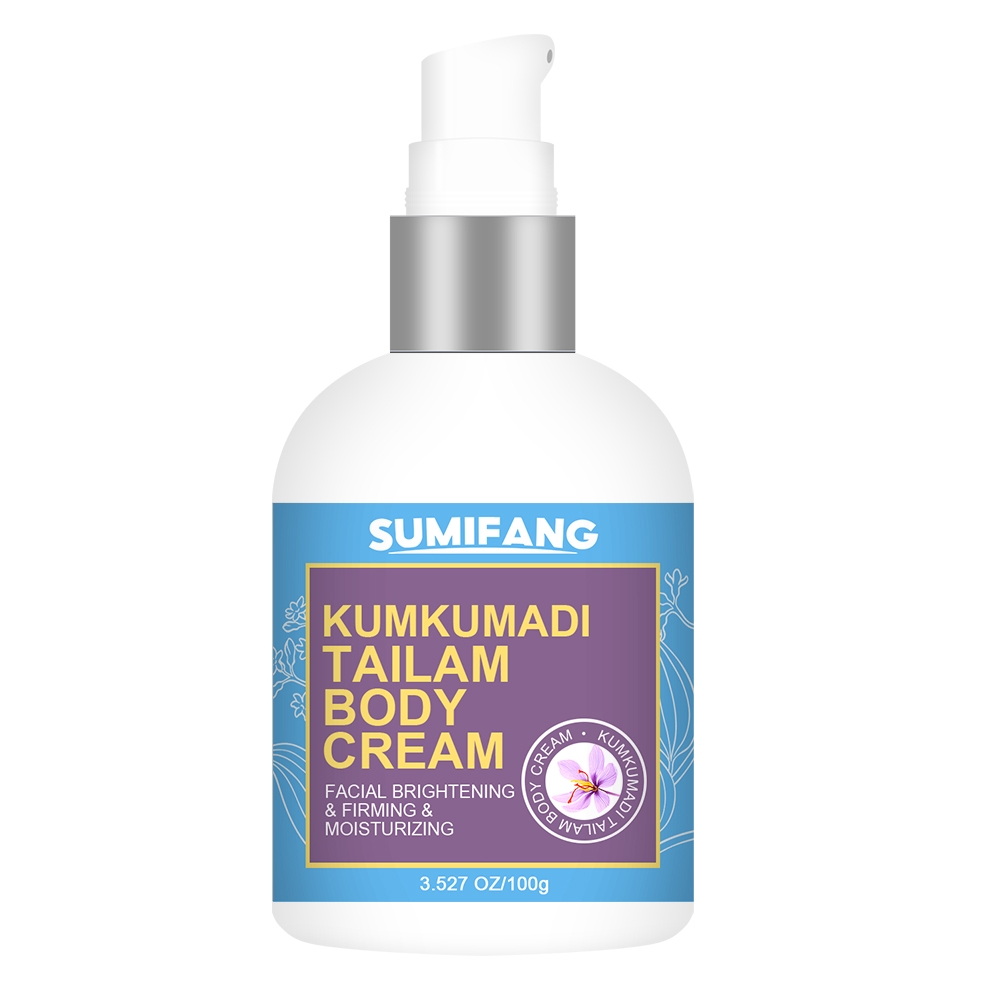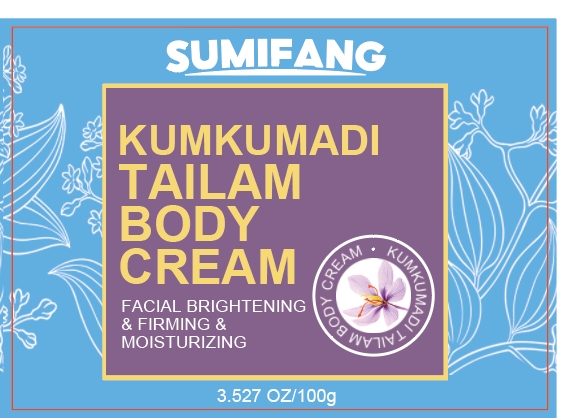 DRUG LABEL: JASMINE BATH BODY MASSAGECREAM
NDC: 84025-124 | Form: CREAM
Manufacturer: Guangzhou Yanxi Biotechnology Co.. Ltd
Category: otc | Type: HUMAN OTC DRUG LABEL
Date: 20240807

ACTIVE INGREDIENTS: GLYCERIN 3 mg/100 g; HYALURONIC ACID 5 mg/100 g
INACTIVE INGREDIENTS: WATER

DOSAGE AND ADMINISTRATION

Cream for moisturizing and brightening body skin

WARNINGS

Keep out of children

INACTIVE INGREDIENT

Aqua

INDICATIONS AND USAGE

For daily body skin care

Keep out of children

PURPOSE

Moisturizes and tightens body skin, gentle and non-irritating to the skin